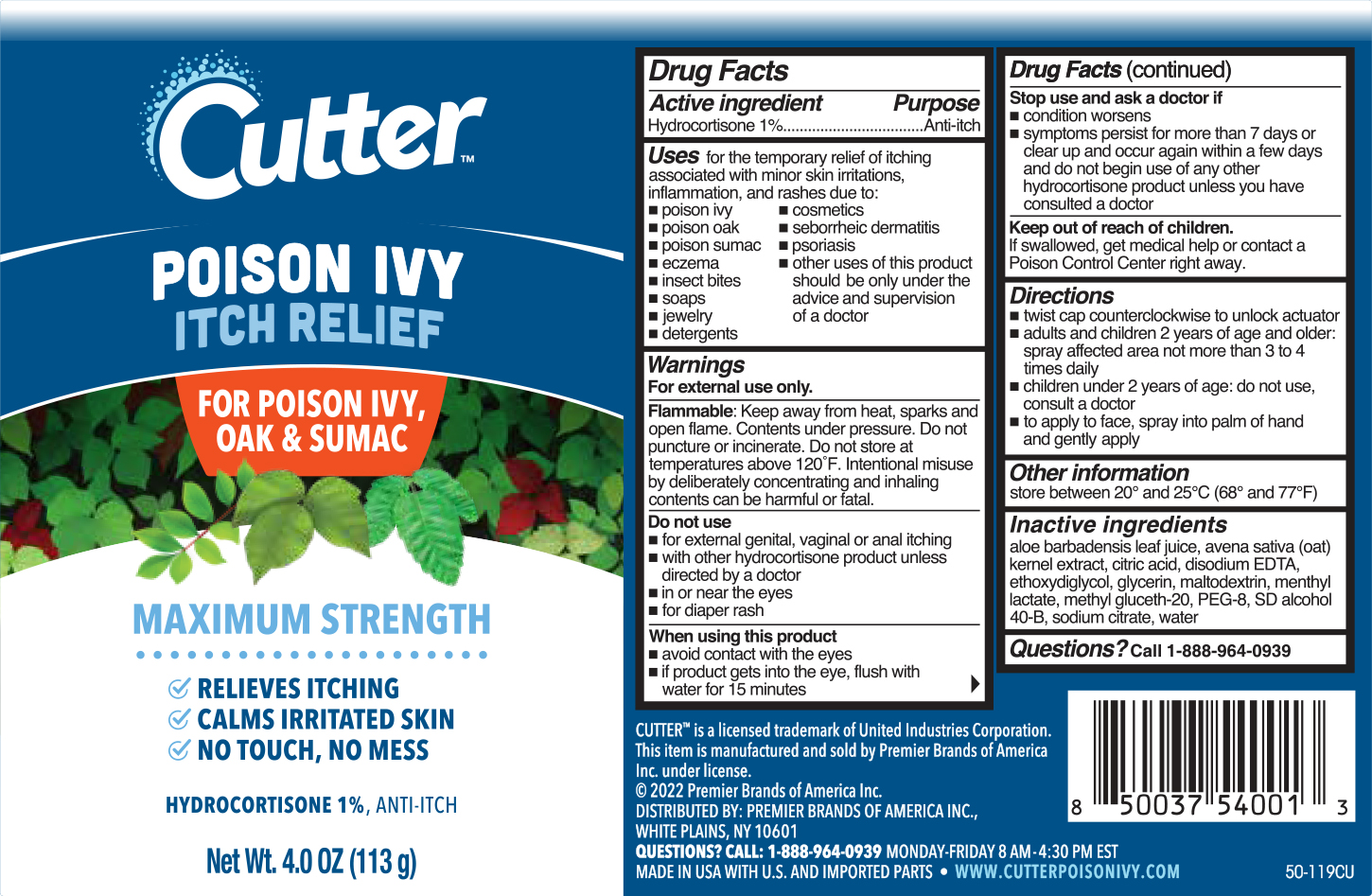 DRUG LABEL: Hydrocortisone
NDC: 56104-250 | Form: AEROSOL, SPRAY
Manufacturer: Premier Brands of America, Inc.
Category: otc | Type: HUMAN OTC DRUG LABEL
Date: 20251027

ACTIVE INGREDIENTS: HYDROCORTISONE 1.13 g/113 g
INACTIVE INGREDIENTS: EDETATE DISODIUM; MENTHYL LACTATE, (-)-; GLYCERIN; POLYETHYLENE GLYCOL 400; SODIUM CITRATE; CITRIC ACID MONOHYDRATE; ALOE VERA LEAF; METHYL GLUCETH-20; OAT; WATER; DIETHYLENE GLYCOL MONOETHYL ETHER; ALCOHOL; MALTODEXTRIN

Cutter Poison Ivy Itch Relief

Active ingredient

Hydrocortisone 1%

Purpose

Anti-itch

Uses

for the temporary relief of itching associated with minor skin irritations, inflammation, and rashes due to:

- eczema
- insect bites
- poison ivy
- poison oak
- poison sumac
- soaps
- jewelry
- detergents
- cosmetics
- seborrheic dermatitis
- psoriasis
- other uses of this product should be only under the advice and supervision of a doctor

Warnings

For external use only.

Flammable:

Keep away from heat, sparks and open flame. Contents under pressure. Do not puncture or incinerate. Do not store at temperatures above 120 ºF. Intentional misuse by deliberately concentrating and inhaling contents can be harmful or fatal.

Do not use

- for external genital, vaginal or anal itching
- with other hydrocortisone product unless directed by a doctor
- in or near the eyes
- for diaper rash

When using this product

- avoid contact with the eyes
- if product gets into the eye, flush with water for 15 minutes

Stop use and ask a doctor if

- condition worsens
- symptoms persist for more than 7 days or clear up and occur again within a few days and do not begin use of any other hydrocortisone product unless you have consulted a doctor

Keep out of the reach of children.

If swallowed, get medical help or contact a Poison Control Center right away.

Directions

- twist cap counterclockwise to unlock actuator
- adults and children 2 years of age and older: spray affected area not more than 3 to 4 times daily
- children under 2 years of age: do not use, consult a doctor
- to apply to face, spray into palm of hand and gently apply

Inactive ingredients

aloe barbadensis leaf juice, avena sativa (oat) kernel extract, citric acid, disodium EDTA, ethoxydiglycol, glycerin, maltodextrin, menthyl lactate, methyl gluceth-20, PEG-8, SD alcohol 40-B, sodium citrate, water

Questions ?

Call 1-866-964-0939

Principal Display Panel

Cutter
Poison Ivy Itch Relief

For Poison Ivy, Oak, & Sumac

Maximum Strength

Relieves Itching

Calms irritated skin

No touch, no mess

HYDROCORTISONE 1% / ANTI-ITCH

NET WT 4.0 0Z (113 g)